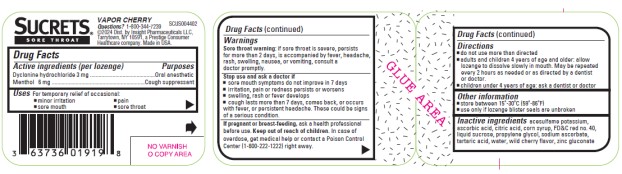 DRUG LABEL: SUCRETS VAPOR CHERRY
NDC: 63736-925 | Form: LOZENGE
Manufacturer: Insight Pharmaceuticals LLC
Category: otc | Type: HUMAN OTC DRUG LABEL
Date: 20241205

ACTIVE INGREDIENTS: DYCLONINE HYDROCHLORIDE 3 mg/1 1; MENTHOL 6 mg/1 1
INACTIVE INGREDIENTS: ACESULFAME POTASSIUM; ASCORBIC ACID; CITRIC ACID MONOHYDRATE; CORN SYRUP; FD&C RED NO. 40; SUCROSE; PROPYLENE GLYCOL; SODIUM ASCORBATE; TARTARIC ACID; WATER; ZINC GLUCONATE

Sucrets Vapor Cherry 63736-925-18

Active ingredient (per lozenge)

Dyclonine hydrochloride 3 mg

Menthol 6 mg

Purpose

Oral anesthetic

Cough suppressant

Uses

For temporary relief of occasional:

- minor irritation
- pain
- sore mouth
- sore throat

Warnings

Sore throat warning: if sore throat is severe, persists for more than 2 days, is accompanied by fever, headache, rash, swelling, nausea, or vomiting, consult a doctor promptly.

Stop use and ask a doctor if

- sore mouth symptoms do not improve in 7 days
- irritation, pain or redness persists or worsens
- swelling, rash or fever develops
- cough lasts more than 7 days, comes back, or occurs with fever, or persistent headache. These could be signs of a serious condition.

If pregnant or breast-feeding,

ask a health professional before use.

Keep out of reach of children.

In case of overdose, get medical help or contact a Poison Control Center (1-800-222-1222) right away.

Directions

- do not use more than directed
- adults and children 4 years of age and older: allow lozenge to dissolve slowly in mouth. May be repeated every 2 hours as needed or as directed by a dentist or doctor.
- children under 4 years of age: ask a dentist or doctor

Other information

- store between 15-30°C (59-86°F)
- use only if lozenge blister seals are unbroken

Inactive ingredients

acesulfame potassium, ascorbic acid, citric acid, corn syrup, fd&c red no. 40, liquid sucrose, propylene glycol, sodium ascorbate, tartaric acid, water, wild cherry flavor, zinc gluconate

PRINCIPAL DISPLAY PANEL

SUCRETS
DYCLONINE / ORAL ANESTHETIC
MENTHOL / COUGH SUPPRESSANT
VAPOR CHERRY
18 LOZENGES